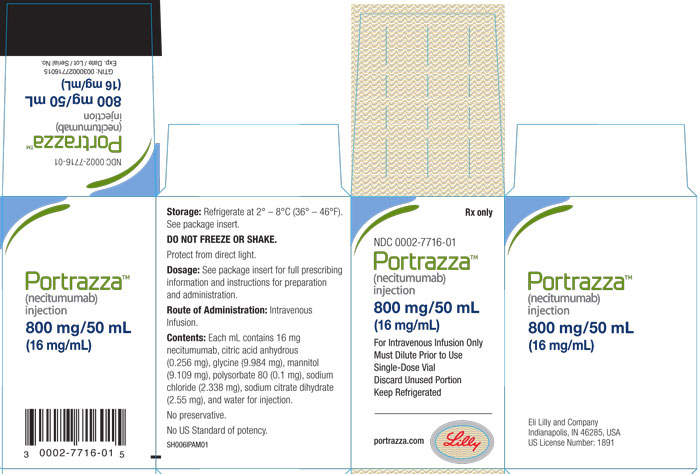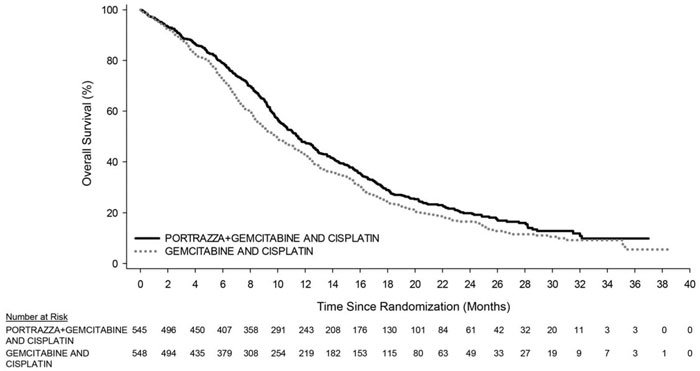 DRUG LABEL: Portrazza
NDC: 0002-7716 | Form: SOLUTION
Manufacturer: Eli Lilly and Company
Category: prescription | Type: HUMAN PRESCRIPTION DRUG LABEL
Date: 20250917

ACTIVE INGREDIENTS: necitumumab 16 mg/1 mL
INACTIVE INGREDIENTS: Anhydrous Citric Acid 0.256 mg/1 mL; Glycine 9.984 mg/1 mL; Mannitol 9.109 mg/1 mL; Polysorbate 80 0.1 mg/1 mL; Sodium Chloride 2.338 mg/1 mL; Trisodium Citrate Dihydrate 2.55 mg/1 mL; Water

HIGHLIGHTS OF PRESCRIBING INFORMATION

These highlights do not include all the information needed to use PORTRAZZA safely and effectively. See full prescribing information for PORTRAZZA.
PORTRAZZA (necitumumab) injection, for intravenous use
Initial U.S. Approval: 2015

WARNING: CARDIOPULMONARY ARREST and HYPOMAGNESEMIA

See full prescription information for complete boxed warning

- Cardiopulmonary arrest and/or sudden death occurred in 3% of patients treated with PORTRAZZA in combination with gemcitabine and cisplatin. Closely monitor serum electrolytes, including serum magnesium, potassium, and calcium, with aggressive replacement when warranted during and after PORTRAZZA administration. (5.1, 5.2)
- Hypomagnesemia occurred in 83% of patients receiving PORTRAZZA in combination with gemcitabine and cisplatin, and was severe in 20%. Monitor patients for hypomagnesemia, hypocalcemia, and hypokalemia prior to each dose of PORTRAZZA during treatment and for at least 8 weeks following completion of PORTRAZZA. Withhold PORTRAZZA for Grade 3 or 4 electrolyte abnormalities. Replete electrolytes as medically appropriate. (5.2)

1 INDICATIONS AND USAGE

PORTRAZZA™ is an epidermal growth factor receptor (EGFR) antagonist indicated, in combination with gemcitabine and cisplatin, for first-line treatment of patients with metastatic squamous non-small cell lung cancer. (1.1)

Limitation of Use: PORTRAZZA is not indicated for treatment of non-squamous non-small cell lung cancer. (1.2, 5.6, 14.2)

2 DOSAGE AND ADMINISTRATION

Recommended dose of PORTRAZZA is 800 mg (absolute dose) as an intravenous infusion over 60 minutes on Days 1 and 8 of each 3-week cycle. (2.1)

3 DOSAGE FORMS AND STRENGTHS

Injection: 800 mg/50 mL (16 mg/mL) solution in a single-dose vial. (3)

4 CONTRAINDICATIONS

None (4)

5 WARNINGS AND PRECAUTIONS

- Cardiopulmonary Arrest: Closely monitor serum electrolytes during and after PORTRAZZA. (5.1)
- Hypomagnesemia: Monitor prior to each infusion and for at least 8 weeks following the completion of PORTRAZZA. Withhold PORTRAZZA for Grade 3 or 4 electrolyte abnormalities; subsequent cycles of PORTRAZZA may be administered in these patients once electrolyte abnormalities have improved to Grade ≤2. Replete electrolytes as necessary. (5.2)
- Venous and Arterial Thromboembolic Events (VTE and ATE): Discontinue PORTRAZZA for severe VTE or ATE. (5.3)
- Dermatologic Toxicities: Monitor for dermatologic toxicities and withhold or discontinue PORTRAZZA for severe toxicity. Limit sun exposure. (2.3, 5.4)
- Infusion-Related Reactions: Monitor for signs and symptoms during and following infusion. Discontinue PORTRAZZA for severe reactions. (2.3, 5.5)
- Increased Toxicity: Non-Squamous NSCLC - Increased toxicity and increased mortality. (5.6)
- Embryo-Fetal Toxicity: Can cause fetal harm. Advise females of reproductive potential of the potential risk to a fetus and to use effective contraception. (5.7, 8.1, 8.3)

6 ADVERSE REACTIONS

The most common adverse reactions (all grades) observed in PORTRAZZA-treated patients at a rate of ≥30% and ≥2% higher than gemcitabine and cisplatin alone arm were rash and hypomagnesemia. (6.1)

To report SUSPECTED ADVERSE REACTIONS, contact Eli Lilly and Company at 1-800-LillyRx (1-800-545-5979) or FDA at 1-800-FDA-1088 or www.fda.gov/medwatch.

8 USE IN SPECIFIC POPULATIONS

Lactation: Do not breastfeed. (8.2)

FULL PRESCRIBING INFORMATION

WARNING: CARDIOPULMONARY ARREST and HYPOMAGNESEMIA

- Cardiopulmonary arrest and/or sudden death occurred in 3.0% of patients treated with PORTRAZZA in combination with gemcitabine and cisplatin. Closely monitor serum electrolytes, including serum magnesium, potassium, and calcium, with aggressive replacement when warranted during and after PORTRAZZA administration [see Warnings and Precautions (5.1, 5.2)].
- Hypomagnesemia occurred in 83% of patients receiving PORTRAZZA in combination with gemcitabine and cisplatin, and was severe in 20% of patients. Monitor patients for hypomagnesemia, hypocalcemia, and hypokalemia prior to each dose of PORTRAZZA during treatment and for at least 8 weeks following completion of PORTRAZZA. Withhold PORTRAZZA for Grade 3 or 4 electrolyte abnormalities. Replete electrolytes as medically appropriate [see Warnings and Precautions (5.2)].

1 INDICATIONS AND USAGE

1.1 Squamous Non-Small Cell Lung Cancer (NSCLC)

PORTRAZZA™ is indicated, in combination with gemcitabine and cisplatin, for first-line treatment of patients with metastatic squamous non-small cell lung cancer.

1.2 Limitation of Use

PORTRAZZA is not indicated for treatment of non-squamous non-small cell lung cancer [see Warnings and Precautions (5.6) and Clinical Studies (14.2)].

2 DOSAGE AND ADMINISTRATION

2.1 Recommended Dose and Schedule

The recommended dose of PORTRAZZA is 800 mg administered as an intravenous infusion over 60 minutes on Days 1 and 8 of each 3-week cycle prior to gemcitabine and cisplatin infusion. Continue PORTRAZZA until disease progression or unacceptable toxicity.

2.2 Premedication

- For patients who have experienced a previous Grade 1 or 2 infusion-related reaction (IRR), pre-medicate with diphenhydramine hydrochloride (or equivalent) prior to all subsequent PORTRAZZA infusions [see Dosage and Administration (2.3)].
- For patients who have experienced a second Grade 1 or 2 occurrence of IRR, pre-medicate for all subsequent infusions, with diphenhydramine hydrochloride (or equivalent), acetaminophen (or equivalent), and dexamethasone (or equivalent) prior to each PORTRAZZA infusion [see Dosage and Administration (2.3)].

2.3 Dose Modifications

Infusion-Related Reactions (IRR)

- Reduce the infusion rate of PORTRAZZA by 50% for Grade 1 IRR [see Dosage and Administration (2.2) and Warnings and Precautions (5.5)].
- Stop the infusion for Grade 2 IRR until signs and symptoms have resolved to Grade 0 or 1; resume PORTRAZZA at 50% reduced rate for all subsequent infusions [see Dosage and Administration (2.2) and Warnings and Precautions (5.5)].
- Permanently discontinue PORTRAZZA for Grade 3 or 4 IRR [see Dosage and Administration (2.2) and Warnings and Precautions (5.5)].

Dermatologic Toxicity

- Withhold PORTRAZZA for Grade 3 rash or acneiform rash until symptoms resolve to Grade ≤2, then resume PORTRAZZA at reduced dose of 400 mg for at least 1 treatment cycle. If symptoms do not worsen, may increase dose to 600 mg and 800 mg in subsequent cycles.
- Permanently discontinue PORTRAZZA if:
  - Grade 3 rash or acneiform rash do not resolve to Grade ≤2 within 6 weeks,
  - Reactions worsen or become intolerable at a dose of 400 mg
  - Patient experiences Grade 3 skin induration/fibrosis [see Warnings and Precautions (5.4) and Adverse Reactions (6.1)] or
  - Grade 4 dermatologic toxicity [see Warnings and Precautions (5.4) and Adverse Reactions (6.1)].

2.4 Preparation for Administration

Inspect vial contents for particulate matter and discoloration prior to dilution [see Description (11)]. Discard the vial if particulate matter or discoloration is identified. Store vials in a refrigerator at 2° to 8°C (36˚ to 46˚F) until time of use. Keep the vial in the outer carton in order to protect from light [see How Supplied/Storage and Handling (16.2)].

- Dilute the required volume of PORTRAZZA with 0.9% Sodium Chloride Injection, USP in an intravenous infusion container to a final volume of 250 mL. Do not use solutions containing dextrose.
- Gently invert the container to ensure adequate mixing.
- DO NOT FREEZE OR SHAKE the infusion solution. DO NOT dilute with other solutions or co-infuse with other electrolytes or medication.
- Store diluted infusion solution for no more than 24 hours at 2° to 8°C (36° to 46°F), or no more than 4 hours at room temperature (up to 25°C [77°F]).
- Discard vial with any unused portion of PORTRAZZA.

2.5 Administration

Visually inspect the diluted solution for particulate matter and discoloration prior to administration. If particulate matter or discoloration is identified, discard the solution.

Administer diluted PORTRAZZA infusion via infusion pump over 60 minutes through a separate infusion line. Flush the line with 0.9% Sodium Chloride Injection, USP at the end of the infusion.

3 DOSAGE FORMS AND STRENGTHS

Injection: 800 mg/50 mL (16 mg/mL) solution in a single-dose vial

4 CONTRAINDICATIONS

None

5 WARNINGS AND PRECAUTIONS

5.1 Cardiopulmonary Arrest

Cardiopulmonary arrest or sudden death occurred in 15 (3%) of 538 patients treated with PORTRAZZA plus gemcitabine and cisplatin as compared to 3 (0.6%) of 541 patients treated with gemcitabine and cisplatin alone in Study 1. Twelve of the fifteen patients died within 30 days of the last dose of PORTRAZZA and had comorbid conditions including history of coronary artery disease (n=3), hypomagnesemia (n=4), chronic obstructive pulmonary disease (n=7), and hypertension (n=5). Eleven of the 12 patients had an unwitnessed death. Patients with significant coronary artery disease, myocardial infarction within 6 months, uncontrolled hypertension, and uncontrolled congestive heart failure were not enrolled in Study 1. The incremental risk of cardiopulmonary arrest or sudden death in patients with a history of coronary artery disease, congestive heart failure, or arrhythmias as compared to those without these comorbid conditions is not known.

Closely monitor serum electrolytes, including serum magnesium, potassium, and calcium prior to each infusion of PORTRAZZA during treatment and after PORTRAZZA administration for at least 8 weeks after the last dose. Withhold PORTRAZZA for Grade 3 or 4 electrolyte abnormalities; subsequent cycles of PORTRAZZA may be administered in these patients once electrolyte abnormalities have improved to Grade ≤2. Replete electrolytes as medically appropriate [see Boxed Warning and Warnings and Precautions (5.2)].

5.2 Hypomagnesemia

Hypomagnesemia occurred in 83% of 461/538 patients with available laboratory results treated with PORTRAZZA as compared to 70% of 457/541 patients with available laboratory results treated with gemcitabine and cisplatin alone in Study 1. Hypomagnesemia was severe (Grade 3 or 4) in 20% of the patients treated with PORTRAZZA compared to 7% of the patients treated with gemcitabine and cisplatin alone. The median time to development of hypomagnesemia and accompanying electrolyte abnormalities was 6 weeks (25th percentile 4 weeks; 75th percentile 9 weeks) after initiation of PORTRAZZA. Monitor patients for hypomagnesemia, hypocalcemia, and hypokalemia prior to each infusion of PORTRAZZA during treatment and for at least 8 weeks following the completion of PORTRAZZA. Withhold PORTRAZZA for Grade 3 or 4 electrolyte abnormalities; subsequent cycles of PORTRAZZA may be administered in these patients once hypomagnesemia and related electrolyte abnormalities have improved to Grade ≤2. Replete electrolytes as medically appropriate [see Boxed Warning, Warnings and Precautions (5.1), and Adverse Reactions (6.1)].

5.3 Venous and Arterial Thromboembolic Events

Venous and arterial thromboembolic events (VTE and ATE), some fatal, were observed with PORTRAZZA in combination with gemcitabine and cisplatin. In Study 1, the incidence of VTE was 9% in patients receiving PORTRAZZA plus gemcitabine and cisplatin versus 5% in patients receiving gemcitabine and cisplatin alone and the incidence of Grade 3 or higher VTE was 5% versus 3%, respectively. The incidence of fatal VTEs was similar between arms (0.2% versus 0.2%). The most common VTEs were pulmonary embolism (5%) and deep-vein thrombosis (2%).

The incidence of ATEs of any grade was 5% versus 4% and the incidence of Grade 3 or higher ATE was 4% versus 2% in the PORTRAZZA containing and gemcitabine and cisplatin arms, respectively, in Study 1. The most common ATEs were cerebral stroke and ischemia (2%) and myocardial infarction (1%).

In an exploratory analysis of Study 1, the relative risk of VTE or ATE was approximately 3-fold higher in patients with a reported history of VTE or ATE than in patients with no reported history of VTE or ATE.

Discontinue PORTRAZZA for patients with serious or life threatening VTE or ATE.

5.4 Dermatologic Toxicities

Dermatologic toxicities, including rash, dermatitis acneiform, acne, dry skin, pruritus, generalized rash, skin fissures, maculo-papular rash and erythema, occurred in 79% of patients receiving PORTRAZZA in Study 1. Skin toxicity was severe in 8% of patients. Skin toxicity usually developed within the first 2 weeks of therapy and resolved within 17 weeks after onset. For Grade 3 skin reactions, modify the dose of PORTRAZZA [see Dosage and Administration (2.3) and Adverse Reactions (6.1)]. Limit sun exposure [see Patient Counseling Information (17)].

Discontinue PORTRAZZA for severe (Grade 4) skin reactions, or for Grade 3 skin induration/fibrosis.

5.5 Infusion-Related Reactions

In Study 1, 1.5% of PORTRAZZA treated patients experienced IRRs of any severity with 0.4% Grade 3 IRR. No patients received premedication for IRR for the first dose of PORTRAZZA in Study 1. Most IRRs occurred after the first or second administration of PORTRAZZA. Monitor patients during and following PORTRAZZA infusion for signs and symptoms of IRR. Discontinue PORTRAZZA for serious or life-threatening IRR [see Dosage and Administration (2.3) and Adverse Reactions (6.1)].

5.6 Non-Squamous NSCLC - Increased Toxicity and Increased Mortality

PORTRAZZA is not indicated for the treatment of patients with non-squamous NSCLC. In a study of PORTRAZZA plus pemetrexed and cisplatin (PC) versus PC alone (Study 2), patients treated with PORTRAZZA and PC experienced more serious (51% versus 41%) and fatal toxicities (16% versus 10%) and cardiopulmonary arrest/sudden death within 30 days of the last study drug (3.3% versus 1.3%) compared to patients who received PC alone [see Clinical Studies (14.2)].

5.7 Embryo-Fetal Toxicity

Based on animal data and its mechanism of action, PORTRAZZA can cause fetal harm when administered to a pregnant woman. Disruption or depletion of EGFR in animal models results in impairment of embryofetal development including effects on placental, lung, cardiac, skin, and neural development. The absence of EGFR signaling has resulted in embryolethality as well as post-natal death in animals. Advise pregnant women of the potential risk to a fetus. Advise females of reproductive potential to use effective contraception during treatment with PORTRAZZA and for three months following the final dose [see Use in Specific Populations (8.1, 8.3) and Clinical Pharmacology (12.1)].

6 ADVERSE REACTIONS

The following adverse drug reactions are discussed in greater detail in other sections of the label:

- Cardiopulmonary Arrest [see Boxed Warning and Warnings and Precautions (5.1)].
- Hypomagnesemia [see Boxed Warning and Warnings and Precautions (5.2)].
- Venous and Arterial Thromboembolic Events [see Warnings and Precautions (5.3)].
- Dermatologic Toxicities [see Dosage and Administration (2.3) and Warnings and Precautions (5.4)].
- Infusion-Related Reactions [see Dosage and Administration (2.2, 2.3) and Warnings and Precautions (5.5)].
- Non-Squamous NSCLC - Increased Toxicity and Increased Mortality [see Warnings and Precautions (5.6) and Clinical Studies (14.2)].

6.1 Clinical Trials Experience

Because clinical trials are conducted under widely varying conditions, adverse reaction rates observed in the clinical trials of a drug cannot be directly compared to rates in the clinical trials of another drug and may not reflect the rates observed in practice.

The safety of PORTRAZZA was evaluated in two randomized, open-label trials comparing PORTRAZZA plus gemcitabine and cisplatin to gemcitabine and cisplatin alone in patients with squamous NSCLC (Study 1), and PORTRAZZA plus pemetrexed and cisplatin to pemetrexed and cisplatin alone in patients with non-squamous NSCLC (Study 2). Since the data in Study 2 demonstrated similar incidence of adverse reactions over control as observed in Study 1, the safety data from Study 1 alone is described below.

For patients who received at least 1 dose of treatment in Study 1, the median age was 62 years (range 32 to 84), 83% were male; 84% were Caucasian; and 92% were smokers. Baseline ECOG performance status was 0 or 1 for 91%, and 2 for 9% of patients; 90% had metastatic disease in 2 or more sites. Patients received PORTRAZZA 800 mg intravenously on days 1 and 8 of each 21 day cycle in combination with up to six cycles of gemcitabine (1250 mg/m^2 on days 1 and 8) and cisplatin (75 mg/m^2 on day 1). Patients received PORTRAZZA until progressive disease or unacceptable toxicity.

Patients in the gemcitabine and cisplatin alone arm received a maximum of 6 cycles, while patients in the PORTRAZZA plus gemcitabine and cisplatin arm demonstrating at least stable disease were permitted to continue to receive additional cycles of PORTRAZZA until disease progression or unacceptable toxicity. The median duration of exposure to PORTRAZZA in 538 patients who received at least 1 dose of treatment in Study 1 was 4.6 months (range 0.5 months to 34 months), including 182 patients exposed for at least 6 months and 41 patients exposed for greater than 1 year. Patients were monitored for safety until 30 days after treatment discontinuation and resolution of treatment-emergent adverse events.

The most common adverse reactions (all grades) observed in PORTRAZZA-treated patients at a rate of ≥15% and ≥2% higher than gemcitabine and cisplatin alone were rash (44%), vomiting (29%), diarrhea (16%), and dermatitis acneiform (15%). The most common severe (Grade 3 or higher) adverse events that occurred at a ≥2% higher rate in PORTRAZZA-treated patients compared to patients treated with gemcitabine and cisplatin alone were venous thromboembolic events (5%; including pulmonary embolism), rash (4%), and vomiting (3%).

Table 1 contains selected adverse drug reactions observed in Study 1 at an incidence of ≥5% in the PORTRAZZA arm and at ≥2% higher incidence than the control arm.

Table 1: Adverse Reactions Occurring at Incidence Rate ≥5% All Grades or a ≥2% Grade 3-4 Difference Between Arms in Patients Receiving PORTRAZZA in Study 1
Adverse Reactions (MedDRA) System Organ Class | PORTRAZZA PLUS GEMCITABINE AND CISPLATIN N=538 (%) |  | GEMCITABINE AND CISPLATIN N=541 (%)
Adverse Reactions (MedDRA) System Organ Class | All Grades (Frequency %) | Grade 3-4 (Frequency %) | All Grades (Frequency %) | Grade 3-4 (Frequency %)
Skin and Subcutaneous Tissue Disorders
Rash | 44 | 4 | 6 | 0.2
Dermatitis Acneiform | 15 | 1 | 0.6 | 0
Acne | 9 | 0.4 | 0.6 | 0
Pruritus | 7 | 0.2 | 0.9 | 0.2
Dry Skin | 7 | 0 | 1 | 0
Skin fissures | 5 | 0.4 | 0 | 0
Gastrointestinal Disorders
Vomiting | 29 | 3 | 25 | 0.9
Diarrhea | 16 | 2 | 11 | 1
Stomatitis | 11 | 1 | 6 | 0.6
Investigations
Weight decreased | 13 | 0.7 | 6 | 0.6
Respiratory, Thoracic and Mediastinal Disorders
Hemoptysis | 10 | 1 | 5 | 0.9
Pulmonary embolisma | 5 | 4 | 2 | 2
Nervous System Disorders
Headache | 11 | 0 | 6 | 0.4
Vascular Disorders
Venous Thromboembolic Events (VTE)b | 9 | 5 | 5 | 3
Infections and Infestations
Paronychia | 7 | 0.4 | 0.2 | 0
Eye Disorders
Conjunctivitisc | 7 | 0.4 | 2 | 0
a Pulmonary embolism is also included in the composite term venous thromboembolic events under system organ class vascular disorders.
b VTE is a composite term which includes: pulmonary embolism, deep vein thrombosis, thrombosis, mesenteric veins thrombosis, pulmonary artery thrombosis, pulmonary venous thrombosis, venous thrombosis limb, axillary vein thrombosis, thrombophlebitis, thrombosis in device, vena cava thrombosis, venous thrombosis, subclavian vein thrombosis, superior vena cava syndrome, and thrombophlebitis superficial.
c Conjunctivitis is a composite term that includes conjunctivitis, eye irritation, vision blurred, conjunctivitis bacterial, dry eye, visual acuity reduced, blepharitis, allergic blepharitis, conjunctiva hemorrhage, eye infection, eye pain, lacrimation increased, ocular hyperemia, Sjogren's syndrome, visual impairment, and eye pruritus.

Clinically relevant adverse reactions (all grades) reported in ≥1% and <5% of patients treated with PORTRAZZA were: dysphagia (3%), oropharyngeal pain (1%), muscle spasms (2%), phlebitis (2%), and hypersensitivity/IRR (1.5%).

In Study 1, 12% of the patients on the PORTRAZZA arm discontinued study treatment due to an adverse reaction. The most common PORTRAZZA related toxicity leading to PORTRAZZA discontinuation was skin rash (1%).

Table 2 contains selected electrolyte abnormalities observed in Study 1 according to laboratory assessment at an incidence of >10% in the PORTRAZZA arm and at >2% higher incidence than the control arm.

The median time to onset of hypomagnesemia was 6 weeks (25th percentile 4 weeks; 75th percentile 9 weeks). Hypomagnesemia was reported as resolved in 43% of the patients who received PORTRAZZA. In Study 1, 32% of the patients in the PORTRAZZA arm and 16% of the patients who received gemcitabine and cisplatin alone received magnesium replacement.

Table 2: Electrolyte Abnormalities according to Laboratory Assessment at Incidence Rate >10% and a >2% Difference between Arms in Patients Receiving PORTRAZZA in Study 1a
LABORATORY PARAMETER | PORTRAZZA PLUS GEMCITABINE AND CISPLATIN N=538 |  |  | GEMCITABINE AND CISPLATIN N=541
LABORATORY PARAMETER | Na | All Grades (Frequency %) | Grade 3 or 4 (Frequency %) | Na | All Grades (Frequency %) | Grade 3 or 4 (Frequency %)
Hypomagnesemia | 461 | 83 | 20 | 457 | 70 | 7
Hypokalemia | 505 | 28 | 5 | 505 | 18 | 3
Hypocalcemia | 502 | 45 | 6 | 499 | 30 | 2
Hypocalcemia (albumin corrected) | 477 | 36 | 4 | 480 | 23 | 2
Hypophosphatemia | 462 | 31 | 8 | 454 | 23 | 6
a Only patients with baseline and at least one post-baseline result are included.

6.2 Immunogenicity

As with all therapeutic proteins, there is the potential for immunogenicity. In clinical trials, treatment-emergent anti-necitumumab antibodies (ADA) were detected in 4.1% (33/814) of patients using an enzyme-linked immunosorbent assay (ELISA). Neutralizing antibodies were detected in 1.4% (11/814) of patients post exposure to PORTRAZZA. No relationship was found between the presence of ADA and incidence of infusion-related reactions. The impact of ADA on efficacy (overall survival) could not be assessed due to the limited number of patients with treatment-emergent ADA. In Study 1, the exposure to necitumumab was lower in patients with ADA post-treatment than in patients without detectable ADA [see Clinical Pharmacology (12.3)].

The detection of antibody formation is highly dependent on the sensitivity and specificity of the assay. Additionally, the observed incidence of antibody (including neutralizing antibody) positivity in an assay may be influenced by several factors including assay methodology, sample handling, timing of sample collection, concomitant medications, and underlying disease. For these reasons, comparison of incidence of antibodies to PORTRAZZA with the incidences of antibodies to other products may be misleading.

8 USE IN SPECIFIC POPULATIONS

8.1 Pregnancy

Risk Summary

Based on animal data and its mechanism of action, PORTRAZZA can cause fetal harm when administered to a pregnant woman [see Clinical Pharmacology (12.1)]. Disruption or depletion of EGFR in animal models results in impairment of embryo-fetal development including effects on placental, lung, cardiac, skin, and neural development. The absence of EGFR signaling has resulted in embryolethality as well as post-natal death in animals (see Data). No animal reproduction studies have been conducted with necitumumab. There are no available data for PORTRAZZA exposure in pregnant women. Advise pregnant women of the potential risk to a fetus, and the risk to postnatal development.

In the U.S. general population, the estimated background risk of major birth defects and miscarriage in clinically recognized pregnancies is 2-4% and 15-20%, respectively.

Data

Animal Data

No animal studies have been conducted to evaluate the effect of necitumumab on reproduction and fetal development; however, based on its mechanism of action, PORTRAZZA can cause fetal harm or developmental anomalies. In mice, EGFR is critically important in reproductive and developmental processes including blastocyst implantation, placental development, and embryo-fetal/postnatal survival and development. Reduction or elimination of embryo-fetal or maternal EGFR signaling can prevent implantation, can cause embryo-fetal loss during various stages of gestation (through effects on placental development) and can cause developmental anomalies and early death in surviving fetuses. Adverse developmental outcomes were observed in multiple organs in embryos/neonates of mice with disrupted EGFR signaling. Human IgG1 is known to cross the placenta; therefore, necitumumab has the potential to be transmitted from the mother to the developing fetus.

In monkeys, administration of a chimeric anti-EGFR antibody that binds to an epitope overlapping that of necitumumab during the period of organogenesis resulted in detectable exposure of the antibody in the amniotic fluid and in the serum of embryos from treated dams. While no fetal malformations or other clear teratogenic effects occurred in offspring, there was an increased incidence of embryolethality and abortions.

8.2 Lactation

Risk Summary

There is no information regarding the presence of necitumumab in human milk, the effects on the breastfed infant, or the effects on milk production. Because of the potential for serious adverse reactions in breastfed infants from PORTRAZZA, advise a nursing woman not to breastfeed during treatment with PORTRAZZA and for three months following the final dose.

8.3 Females and Males of Reproductive Potential

Contraception

Females

Based on its mechanism of action, PORTRAZZA can cause fetal harm when administered to a pregnant woman [see Use in Specific Populations (8.1)]. Advise females of reproductive potential to use effective contraception during treatment with PORTRAZZA and for three months following the final dose.

8.4 Pediatric Use

The safety and effectiveness of PORTRAZZA have not been established in pediatric patients.

8.5 Geriatric Use

Of the 545 patients in the PORTRAZZA plus gemcitabine and cisplatin arm in Study 1, 213 (39%) were 65 years and over, while 108 (20%) were 70 years and over. In an exploratory subgroup analysis of Study 1, the hazard ratio for overall survival in patients 70 years or older was 1.03 (95% CI: 0.75, 1.42). Of the adverse reactions listed in Table 1 [see Adverse Reactions (6.1)], there was a higher incidence (≥3%) of venous thromboembolic events including pulmonary embolism in patients age 70 and over compared to those who were younger than age 70.

8.6 Renal Impairment

No formal studies have been conducted to evaluate the effect of renal impairment on the exposure to necitumumab. Renal function has no influence on the exposure to necitumumab based on the population pharmacokinetic analysis of data from clinical trials [see Clinical Pharmacology (12.3)].

8.7 Hepatic Impairment

No formal studies have been conducted to evaluate the effect of hepatic impairment on the exposure to necitumumab. Mild or moderate hepatic impairment has no influence on the exposure to necitumumab based on the population pharmacokinetic analysis. No patients with severe hepatic impairment were enrolled in the clinical trials with PORTRAZZA [see Clinical Pharmacology (12.3)].

10 OVERDOSAGE

There has been limited experience with PORTRAZZA overdose in human clinical trials.

The highest dose of PORTRAZZA studied clinically in a human dose-escalation Phase 1 study was 1000 mg once a week and once every other week. Two out of 9 patients in the every other week cohort experienced dose-limiting toxicities (e.g., a combination of Grade 3 headache, vomiting, and nausea). There is no known antidote for PORTRAZZA overdose.

11 DESCRIPTION

Necitumumab is an anti-EGFR recombinant human monoclonal antibody of the IgG1 kappa isotype that specifically binds to the ligand binding site of the human EGFR. Necitumumab has an approximate molecular weight of 144.8 kDa. Necitumumab is produced in genetically engineered mammalian NS0 cells.

PORTRAZZA is a sterile, preservative free, clear to slightly opalescent and colorless to slightly yellow solution. PORTRAZZA is available in single-dose vials for intravenous infusion following dilution. Each vial contains 800 mg PORTRAZZA in 50 mL (16 mg/mL).

Each mL contains necitumumab (16 mg), citric acid anhydrous (0.256 mg), glycine (9.984 mg), mannitol (9.109 mg), polysorbate 80 (0.1 mg), sodium chloride (2.338 mg), sodium citrate dihydrate (2.55 mg), and water for injection, pH 6.0.

12 CLINICAL PHARMACOLOGY

12.1 Mechanism of Action

Necitumumab is a recombinant human lgG1 monoclonal antibody that binds to the human epidermal growth factor receptor (EGFR) and blocks the binding of EGFR to its ligands. Expression and activation of EGFR has been correlated with malignant progression, induction of angiogenesis, and inhibition of apoptosis. Binding of necitumumab induces EGFR internalization and degradation in vitro. In vitro, binding of necitumumab also led to antibody-dependent cellular cytotoxicity (ADCC) in EGFR-expressing cells.

In in vivo studies using xenograft models of human cancer, including non-small cell lung carcinoma, administration of necitumumab to implanted mice resulted in increased antitumor activity in combination with gemcitabine and cisplatin as compared to mice receiving gemcitabine and cisplatin alone.

12.3 Pharmacokinetics

Based on population pharmacokinetic (popPK) analysis of serum concentration data from patients in clinical studies with PORTRAZZA, necitumumab exhibits dose-dependent kinetics. Following the administration of PORTRAZZA 800 mg on Days 1 and 8 of each 21 day cycle, the estimated mean total systemic clearance (CLtot) at steady state is 14.1 mL/h (CV=39%), the steady state volume of distribution (Vss) is 7.0 L (CV=31%) and the elimination half-life is approximately 14 days. The predicted time to reach steady state is approximately 100 days.

Specific Populations

Effect of Age, Body Weight, Sex and Race:

Based on the popPK analysis with data obtained in 807 patients, age (range 19-84 years), sex (75% males), and race (85% Whites) have no effect on the systemic exposure of necitumumab.

Body weight is identified as a covariate in the popPK analysis; however, weight-based dosing is not expected to significantly decrease the variability in exposure. No dose adjustment based on body weight is necessary.

Renal Impairment

Patients with Renal Impairment — PopPK analysis did not identify a correlation between necitumumab exposure and renal function as assessed by estimated creatinine clearance ranging from 11-250 mL/min.

Hepatic Impairment

Patients with Hepatic Impairment — PopPK analysis did not identify a correlation between the exposure of necitumumab and hepatic function as assessed by alanine aminotransferase (ranging from 2-615 U/L), aspartate transaminase (ranging from 1.2-619 U/L) and total bilirubin (ranging from 0.1-106 μmol/L).

Drug Interactions

Effect of Necitumumab on Gemcitabine and Cisplatin

In 12 patients with advanced solid tumors who received gemcitabine and cisplatin in combination with PORTRAZZA, the geometric mean dose-normalized AUC of gemcitabine was increased by 22% and Cmax increased by 63% compared to administration of gemcitabine and cisplatin alone while exposure to cisplatin was unchanged.

Effect of Gemcitabine and Cisplatin on Necitumumab

Concomitant administration of gemcitabine and cisplatin had no effect on the exposure of necitumumab.

Immunogenicity

In Study 1, the CLtot of necitumumab was 26% higher and Css,ave was 34% lower in patients who tested positive for anti-necitumumab antibodies (ADA) post-treatment than patients who tested negative for ADA post-treatment.

13 NONCLINICAL TOXICOLOGY

13.1 Carcinogenesis, Mutagenesis, Impairment of Fertility

No studies have been performed to assess the potential of necitumumab for carcinogenicity or genotoxicity.

Fertility studies have not been performed with necitumumab.

14 CLINICAL STUDIES

14.1 Squamous Non-Small Cell Lung Cancer

Study 1 was a randomized, multi-center open-label, controlled trial conducted in 1093 patients receiving gemcitabine and cisplatin first-line chemotherapy for metastatic squamous NSCLC. Patients were randomized (1:1) to receive PORTRAZZA plus gemcitabine and cisplatin or gemcitabine and cisplatin alone. Stratification factors were ECOG performance status (0, 1 versus 2) and geographic region (North America, Europe, and Australia versus South America, South Africa, and India versus Eastern Asia). Gemcitabine (1250 mg/m^2, Days 1 and 8) plus cisplatin (75 mg/m^2, Day 1) were administered every 3 weeks (1 cycle) for a maximum of 6 cycles in the absence of disease progression or unacceptable toxicity. PORTRAZZA (800 mg by intravenous infusion on Days 1 and 8 of each 3-week cycle) was administered prior to gemcitabine and cisplatin. Patients demonstrating at least stable disease on PORTRAZZA plus gemcitabine and cisplatin were to continue PORTRAZZA as a single agent in the absence of disease progression or unacceptable toxicity after completion of 6 planned courses of chemotherapy or if chemotherapy was discontinued for toxicity.

Of the 1093 randomized patients, the median age was 62 years (range 32 to 86), 83% were male; 84% were Caucasian; and 91% were smokers. The majority of the patients (87%) were enrolled in North America, Europe and Australia, 36 patients (3%) were enrolled at clinical sites in the U.S., 6% of the patients were enrolled in South America, South Africa and India and 8% enrolled at clinical sites in Eastern Asia. Baseline ECOG performance status was 0 or 1 for 91%, and 2 for 9% of patients; 91% had metastatic disease in 2 or more sites. In the PORTRAZZA plus gemcitabine and cisplatin arm, 51% of patients continued PORTRAZZA after completion or discontinuation of chemotherapy. Use of post-study systemic therapy was 47% in the PORTRAZZA plus gemcitabine and cisplatin arm, and 45% in the gemcitabine and cisplatin arm.

The main outcome measure was overall survival (OS). Investigator-assessed progression-free survival (PFS) and overall response rate (ORR) were also assessed. Overall survival and PFS were statistically significantly improved in patients randomized to receive PORTRAZZA plus gemcitabine and cisplatin compared to gemcitabine and cisplatin alone. There was no difference in ORR between arms, with an ORR of 31% (95% CI 27, 35) for PORTRAZZA plus gemcitabine and cisplatin arm and an ORR of 29% (95% CI 25, 33) for gemcitabine and cisplatin arm, p-value 0.40.

Efficacy results are shown in Table 3 and Figure 1.

Table 3: Efficacy Results for Metastatic Squamous Non-Small Cell Lung Cancer
 | PORTRAZZA PLUS GEMCITABINE AND CISPLATIN N=545 | GEMCITABINE AND CISPLATIN N=548
Overall Survival
Number of deaths (%) | 418 (77%) | 442 (81%)
Median – months (95% CI)a | 11.5 (10.4, 12.6) | 9.9 (8.9, 11.1)
Stratified Hazard Ratio (95% CI) | 0.84 (0.74, 0.96)
Stratified Log-rank p-value | 0.01
Progression-Free Survivalb
Number of events (%) | 431 (79%) | 417 (76%)
Median – months (95% CI) | 5.7 (5.6, 6.0) | 5.5 (4.8, 5.6)
Stratified Hazard Ratio (95% CI) | 0.85 (0.74, 0.98)
Stratified Log-rank p-value | 0.02
a Abbreviations: CI = confidence interval
b Investigator assessed

Figure 1: Kaplan-Meier Curves of Overall Survival in Patients with Metastatic Squamous Non-Small Cell Lung Cancer

14.2 Non-Squamous NSCLC - Lack of Efficacy

Lack of efficacy of PORTRAZZA in combination with pemetrexed and cisplatin for the treatment of patients with metastatic non-squamous non-small cell lung cancer was determined in one randomized, open-label, multicenter trial (Study 2). The study was closed prematurely after 633 patients were enrolled due to increased incidence of death due to any cause and of thromboembolic events in the PORTRAZZA arm. Patients with no prior chemotherapy for metastatic disease were randomized (1:1) to receive PORTRAZZA plus pemetrexed and cisplatin or pemetrexed and cisplatin alone. Stratification factors were smoking status (non-smokers versus light smokers versus smokers), ECOG performance status (0 - 1 versus 2), histology (adenocarcinoma/large cell versus others), and geographic region. PORTRAZZA (800 mg, Days 1 and 8 of each 3-week cycle) was administered prior to pemetrexed and cisplatin. Patients demonstrating at least stable disease on PORTRAZZA plus pemetrexed and cisplatin were to continue PORTRAZZA as a single agent in the absence of disease progression or unacceptable toxicity after completion of 6 planned courses of chemotherapy.

Of the 633 patients, 315 were randomized to PORTRAZZA plus pemetrexed and cisplatin arm and 318 in the pemetrexed and cisplatin arm. The median age was 61 years, 67 % were male, 93% were Caucasian and 94% had ECOG PS 0 or 1. More than 75% were smokers and 89% had adenocarcinoma histology.

The main efficacy outcome was OS. Progression-free survival and ORR were also assessed. Addition of PORTRAZZA to pemetrexed and cisplatin did not improve OS [HR=1.01; 95%CI (0.84, 1.21); p-value = 0.96)]; PFS [HR=0.96; 95% CI (0.8, 1.16)] or ORR (31% in the PORTRAZZA plus pemetrexed and cisplatin arm and 32% in the pemetrexed and cisplatin alone arm).

16 HOW SUPPLIED/STORAGE AND HANDLING

16.1 How Supplied

PORTRAZZA is supplied in single-dose vials as a sterile, preservative-free solution:

- 800 mg/50 mL (16 mg/mL) NDC 0002-7716-01

16.2 Storage and Handling

Store vials in a refrigerator at 2° to 8°C (36° to 46°F) until time of use. Keep the vial in the outer carton in order to protect from light. DO NOT FREEZE OR SHAKE the vial.

17 PATIENT COUNSELING INFORMATION

Hypomagnesemia

Advise patients of risk of decreased blood levels of magnesium, potassium and calcium. Take medicines to replace the electrolytes exactly as advised by the physician. [see Boxed Warning and Warnings and Precautions (5.2)]

Venous and Arterial Thromboembolic Events

Advise patients of increased risk of venous and arterial thromboembolic events [see Warnings and Precautions (5.3)].

Skin reactions

Advise patients to minimize sun exposure with protective clothing and use of sunscreen while receiving PORTRAZZA [see Dosage and Administration (2.3) and Warnings and Precautions (5.4)].

Infusion-Related Reactions

Advise patients to report signs and symptoms of infusion reactions such as fever, chills, or breathing problems [see Warnings and Precautions (5.5)].

Embryo-Fetal Toxicity

Advise pregnant women of the potential risk to a fetus [see Use in Specific Populations (8.1)].

Advise females of reproductive potential to use effective contraception during treatment with PORTRAZZA and for three months following final dose [see Use in Specific Populations (8.3)].

Lactation

Advise women not to breastfeed during treatment with PORTRAZZA and for three months following the final dose [see Use in Specific Populations (8.2)].

Literature issued November 2015

Manufactured by: Eli Lilly and Company, Indianapolis, IN 46285
US License No. 1891
Marketed by: Lilly USA, LLC, Indianapolis, IN 46285, USA

Copyright © 2015, Eli Lilly and Company. All rights reserved.

POR-0001-USPI-20151124

PORTRAZZA 800mg Single Dose Vial

Rx only

NDC 0002-7716-01

Portrazza™

(necitumumab) injection

800 mg/50 mL

(16 mg/mL)

For Intravenous Infusion Only

Must Dilute Prior to Use

Single-Dose Vial

Discard Unused Portion

Keep Refrigerated

portrazza.com

Lilly